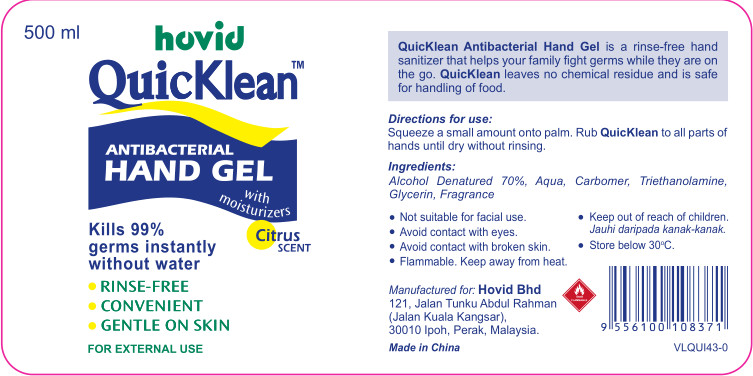 DRUG LABEL: Lvjing brand disinfectant
NDC: 52985-001 | Form: GEL
Manufacturer: Anhui Lvzhou Disinfection Products Co., Ltd
Category: otc | Type: HUMAN OTC DRUG LABEL
Date: 20200407

ACTIVE INGREDIENTS: ALCOHOL 350 mL/500 mL
INACTIVE INGREDIENTS: GLYCERIN; TROLAMINE; FRAGRANCE LAVENDER & CHIA F-153480; WATER; CARBOMER HOMOPOLYMER, UNSPECIFIED TYPE

DOSAGE AND ADMINISTRATION

Store below 30 o C

INACTIVE INGREDIENT

Aqua

Carbomer

Triethanolamine

Glycerin

Fragrance

INDICATIONS AND USAGE

Not suitable for facial use.
Avoid contact with eyes.
Avoid contact with broken skin.
Flammable. Keep away from hea

ACTIVE INGREDIENT

Alcohol

keep out of children

PURPOSE

Disinfection
Sterilization
No Rinseing

WARNINGS

Not suitable for facial use.
Avoid contact with eyes.
Avoid contact with broken skin.
Flammable. Keep away from heat

Keep out of reach of children.Jauhi daripada kanak-kanak.
Store below 30 o C.